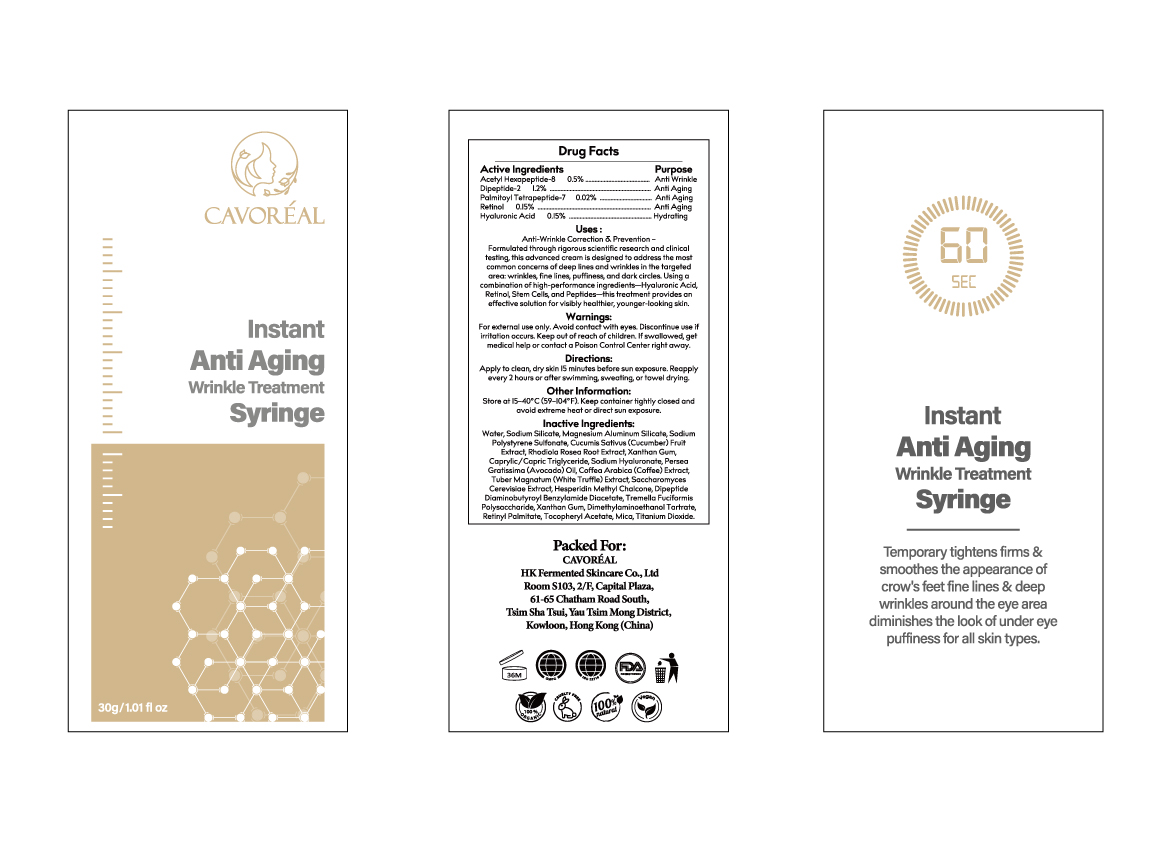 DRUG LABEL: Instant Anti Aging Wrinkle Eye Treatment Syringe
NDC: 87036-034 | Form: CREAM
Manufacturer: Guangzhou Meijiao Medical Biotechnology Co., Ltd.
Category: otc | Type: HUMAN OTC DRUG LABEL
Date: 20251121

ACTIVE INGREDIENTS: HYALURONIC ACID 0.045 g/30 g; ACETYL HEXAPEPTIDE-8 0.15 g/30 g; DIPEPTIDE-2 0.36 g/30 g; PALMITOYL TETRAPEPTIDE-7 0.006 g/30 g; RETINOL 0.045 g/30 g
INACTIVE INGREDIENTS: HESPERIDIN METHYL CHALCONE; DIPEPTIDE DIAMINOBUTYROYL BENZYLAMIDE DIACETATE; TITANIUM DIOXIDE; RETINYL PALMITATE; SODIUM POLYSTYRENE SULFONATE; TREMELLA FUCIFORMIS WHOLE; WATER; SODIUM SILICATE; RHODIOLA ROSEA ROOT; CAPRYLIC/CAPRIC TRIGLYCERIDE; SODIUM HYALURONATE; PERSEA GRATISSIMA (AVOCADO) OIL; COFFEA ARABICA (COFFEE) SEED OIL; TUBER MAGNATUM WHOLE; TOCOPHERYL SUCCINATE; MICA; MAGNESIUM ALUMINUM SILICATE; CUCUMIS SATIVUS (CUCUMBER) FRUIT; XANTHAN GUM; SACCHAROMYCES CEREVISIAE; DIMETHYLAMINOETHANOL TARTRATE

Uses:

Anti-Wrinkle Correction & Prevention –
Formulated through rigorous scientific research and clinical testing, this advanced cream is designed to address the most common concerns of deep lines and wrinkles in the targeted area: wrinkles, fine lines, puffiness, and dark circles. Using a combination of high-performance ingredients—Hyaluronic Acid, Retinol, Stem Cells, and Peptides—this treatment provides an effective solution for visibly healthier, younger-looking skin.

Warnings:

For external use only. Avoid contact with eyes. Discontinue use if irritation occurs. Keep out of reach of children.
If swallowed, get medical help or contact a Poison Control Center right away.

Warnings:

For external use only. Avoid contact with eyes. Discontinue use if irritation occurs. Keep out of reach of children.
If swallowed, get medical help or contact a Poison Control Center right away.

Active Ingredients – Purpose

Acetyl Hexapeptide-8 …… 0.5% …… Anti Wrinkle
Dipeptide-2 …… 1.2% …… Anti Aging
Palmitoyl Tetrapeptide-7 …… 0.02% …… Anti Aging
Retinol …… 0.15% …… Anti Aging
Hyaluronic Acid …… 0.15% …… Hydrating

Inactive Ingredients:

Water, Sodium Silicate, Magnesium Aluminum Silicate, Sodium Polystyrene Sulfonate, Cucumis Sativus (Cucumber) Fruit Extract, Rhodiola Rosea Root Extract, Xanthan Gum, Caprylic/Capric Triglyceride, Sodium Hyaluronate, Persea Gratissima (Avocado) Oil, Coffea Arabica (Coffee) Extract, Tuber Magnatum (White Truffle) Extract, Saccharomyces Cerevisiae Extract, Hesperidin Methyl Chalcone, Dipeptide Diaminobutyroyl Benzylamide Diacetate, Tremella Fuciformis Polysaccharide, Xanthan Gum, Dimethylaminoethanol Tartrate, Retinyl Palmitate, Tocopheryl Acetate, Mica, Titanium Dioxide.

Directions:

Apply to clean, dry skin 15 minutes before sun exposure.
Reapply every 2 hours or after swimming, sweating, or towel drying.

Other Information:

Store at 15–40°C (59–104°F). Keep container tightly closed and avoid extreme heat or direct sun exposure.

Directions:

Apply to clean, dry skin 15 minutes before sun exposure.
Reapply every 2 hours or after swimming, sweating, or towel drying.

WHEN USING

Apply to clean, dry skin 15 minutes before sun exposure.
Reapply every 2 hours or after swimming, sweating, or towel drying.

Warnings:

For external use only. Avoid contact with eyes. Discontinue use if irritation occurs. Keep out of reach of children.
If swallowed, get medical help or contact a Poison Control Center right away.

Warnings:

For external use only. Avoid contact with eyes. Discontinue use if irritation occurs. Keep out of reach of children.
If swallowed, get medical help or contact a Poison Control Center right away.

Uses:

Anti-Wrinkle Correction & Prevention –
Formulated through rigorous scientific research and clinical testing, this advanced cream is designed to address the most common concerns of deep lines and wrinkles in the targeted area: wrinkles, fine lines, puffiness, and dark circles. Using a combination of high-performance ingredients—Hyaluronic Acid, Retinol, Stem Cells, and Peptides—this treatment provides an effective solution for visibly healthier, younger-looking skin.